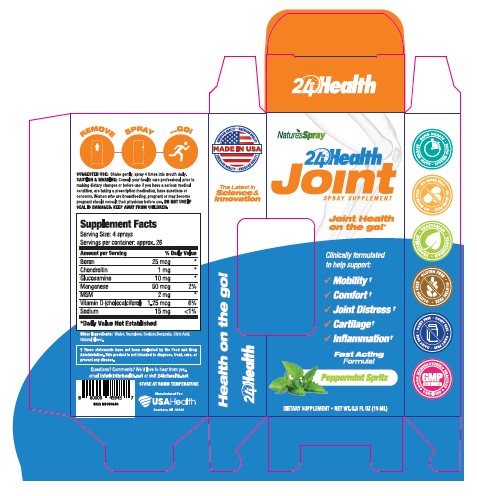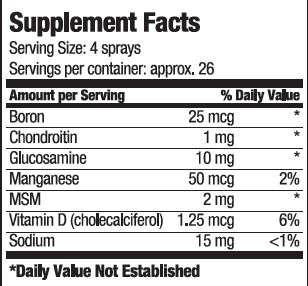 DRUG LABEL: 24hr Health Joint
NDC: 80893-008 | Form: SPRAY
Manufacturer: USA Health
Category: other | Type: Dietary Supplement
Date: 20201106

ACTIVE INGREDIENTS: BORON 25 ug/15 mL; CHONDROITIN SULFATE SODIUM (BOVINE) 1 mg/15 mL; GLUCOSAMINE 10 mg/15 mL; MANGANESE 50 ug/15 mL; VITAMIN D 1.25 ug/15 mL; SODIUM 15 mg/15 mL; DIMETHYL SULFONE 2 mg/15 mL
INACTIVE INGREDIENTS: Water; Sucralose; SODIUM BENZOATE; CITRIC ACID MONOHYDRATE

24hr Health Joint

Purpose

Clinically formulated to help support:

- Mobility
- Comfort
- Joint Distress
- Cartilage
- Inflammation

Precaution

Consult your health care professional prior to making dietary changes or before use if you have a serious medical condition, are taking a prescription medicine, have questions or concerns.

Warnings

Women who are breastfeeding, pregnant, or may become pregnant should consult their physician before use.

Safe Handling

Do not use if seal is damaged. Keep away from children.

Dosage

Shake gently. Spray 4 times into mouth daily.